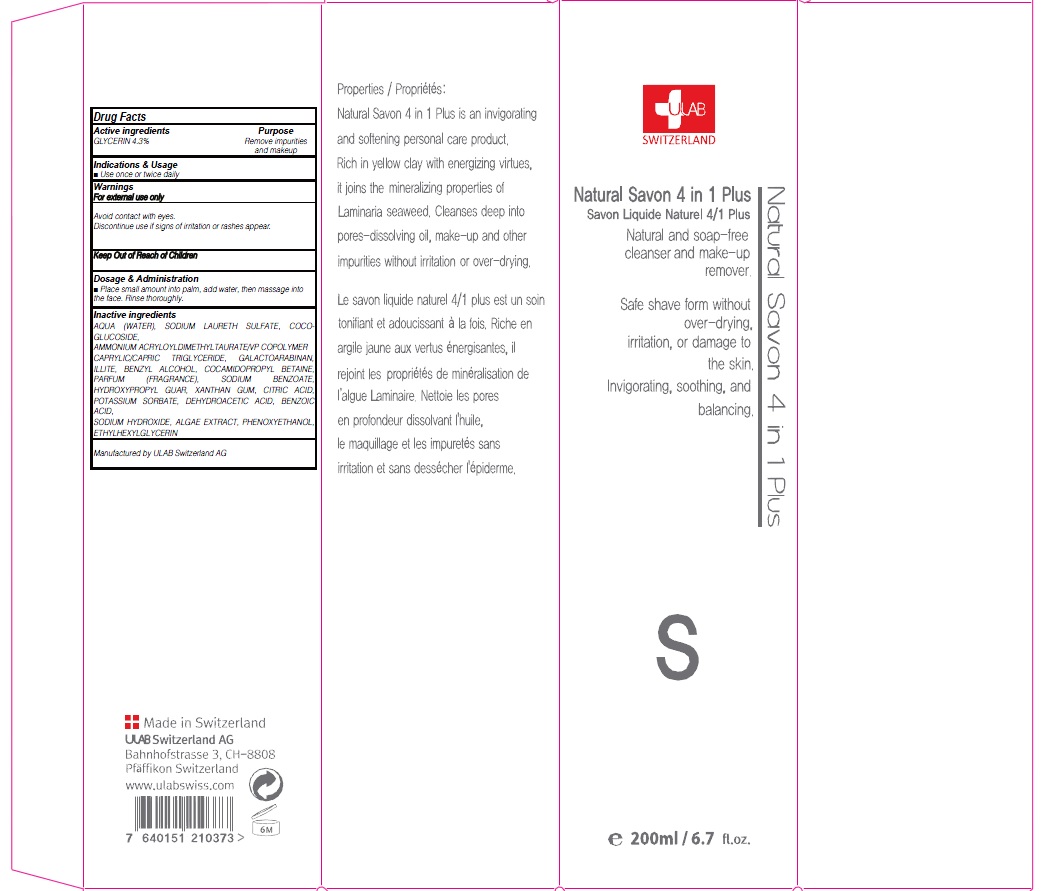 DRUG LABEL: NATURAL SAVON 4IN1 PLUS
NDC: 71276-020 | Form: CREAM
Manufacturer: ULAB
Category: otc | Type: HUMAN OTC DRUG LABEL
Date: 20170321

ACTIVE INGREDIENTS: GLYCERIN 8.6 g/200 mL
INACTIVE INGREDIENTS: WATER; SODIUM LAURETH SULFATE

ACTIVE INGREDIENT

Active ingredients: GLYCERIN 4.3%

INACTIVE INGREDIENT

Inactive ingredients: AQUA (WATER), SODIUM LAURETH SULFATE, COCO-GLUCOSIDE, AMMONIUM ACRYLOYLDIMETHYLTAURATE/VP COPOLYMER CAPRYLIC/CAPRIC TRIGLYCERIDE, GALACTOARABINAN, ILLITE, BENZYL ALCOHOL, COCAMIDOPROPYL BETAINE, PARFUM (FRAGRANCE), SODIUM BENZOATE, HYDROXYPROPYL GUAR, XANTHAN GUM, CITRIC ACID, POTASSIUM SORBATE, DEHYDROACETIC ACID, BENZOIC ACID, SODIUM HYDROXIDE, ALGAE EXTRACT, PHENOXYETHANOL, ETHYLHEXYLGLYCERIN

PURPOSE

Purpose: Remove impurities and makeup

WARNINGS

Warnings: For external use only Avoid contact with eyes. Discontinue use if signs of irritation or rashes appear.

KEEP OUT OF REACH OF CHILDREN

INDICATIONS & USAGE

Indications & Usage: Use once or twice daily

DOSAGE & ADMINISTRATION

Dosage & Administration: Place small amount into palm, add water, then massage into the face. Rinse thoroughly.